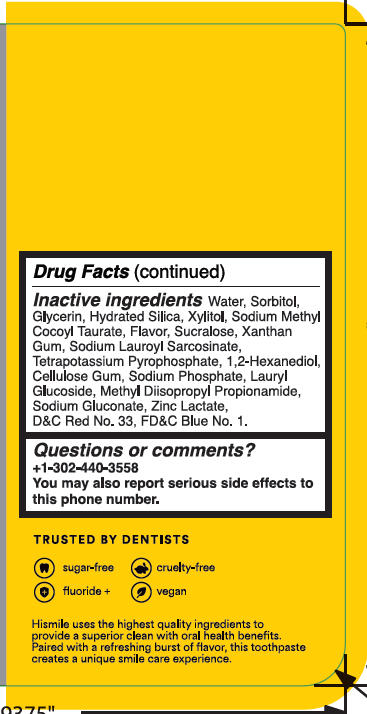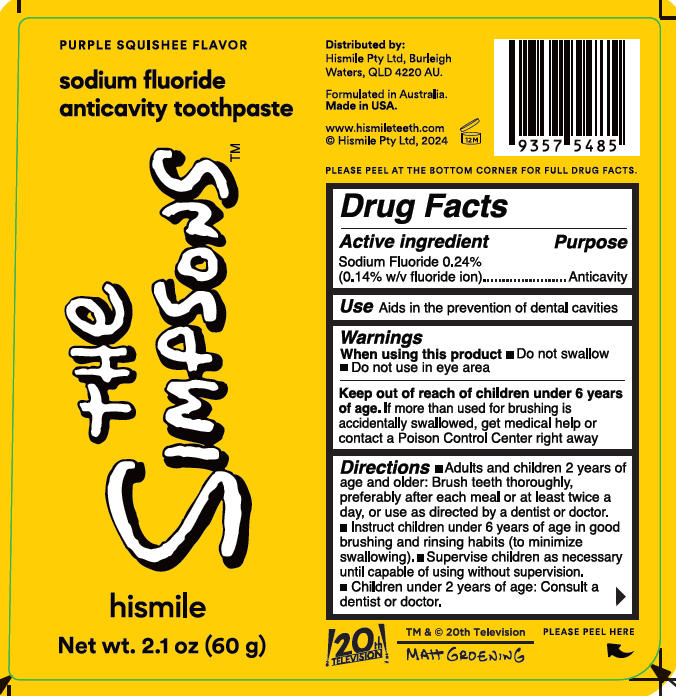 DRUG LABEL: The Simpsons Purple Squishee Flavor Sodium Fluoride Anticavity Toothpast
NDC: 83013-346 | Form: GEL
Manufacturer: HISMILE PTY LTD
Category: otc | Type: HUMAN OTC DRUG LABEL
Date: 20250903

ACTIVE INGREDIENTS: SODIUM FLUORIDE 0.243 g/100 g
INACTIVE INGREDIENTS: POTASSIUM PYROPHOSPHATE; SODIUM GLUCONATE; FD&C BLUE NO. 1; CELLULOSE GUM; WATER; XYLITOL; LAURYL GLUCOSIDE; METHYL DIISOPROPYL PROPIONAMIDE; SUCRALOSE; D&C RED NO. 33; XANTHAN GUM; SORBITOL; GLYCERIN; SODIUM LAUROYL SARCOSINATE; 1,2-HEXANEDIOL; SODIUM PHOSPHATE; ZINC LACTATE; HYDRATED SILICA; SODIUM METHYL COCOYL TAURATE

The Simpsons Purple Squishee Flavor Sodium Fluoride Anticavity Toothpaste

Active ingredient

Sodium Fluoride 0.24%

(0.14 w/v fluoride ion)

Purpose

Anticavity

Use

Aids in the prevention of dental cavities

Warnings

When using this product

Do not swallow

Do not use in eye area

Keep out of reach of children under 6 years old of age. If more than used for brushing is accidentally swallowed, get medical help or contact a Poison Control Center right away.

Directions

- Adults and children 2 years of age and older: Brush teeth thoroughly, preferably after each meal or at least twice a day, or use as directed by a dentist or doctor.
- Instruct children under 6 years of age in good brushing and rinsing habits (to minimize swallowing).
- Supervise children as necessary until capable of using without supervision.
- Children under 2 years of age: Consult a dentist or doctor.

Inactive ingredients

Water

Sorbitol

Glycerin

Hydrated Silica

Xylitol

Sodium methyl cocoyl taurate

Flavor

Sucralose

Xanthan Gum

Sodium Lauroyl Sarcosinate

Tetrapotassium Phosphate

1,2-Hexanediol

Cellulose Gum

Sodium Phosphate

Lauryl Glucoside

Methyl Diisopropyl Propionamide

Sodium Gluconate

Zinc Lactate

D&C Red No. 33

FD&C Blue No. 1

Questions or comments

+1-302-440-3558

You may also report serious side effects to this phone number.